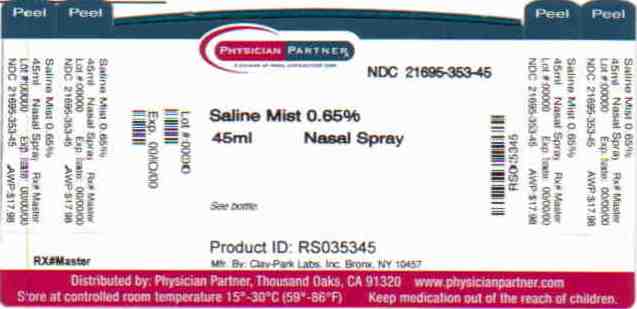 DRUG LABEL: Saline Mist
NDC: 21695-353 | Form: SPRAY
Manufacturer: Rebel Distributors Corp
Category: otc | Type: HUMAN OTC DRUG LABEL
Date: 20110221

ACTIVE INGREDIENTS: SODIUM CHLORIDE 6.5 mg/1 mL
INACTIVE INGREDIENTS: WATER; SODIUM PHOSPHATE, DIBASIC, DIHYDRATE; BENZYL ALCOHOL; SODIUM PHOSPHATE, MONOBASIC ANHYDROUS; BENZALKONIUM CHLORIDE

Saline Mist Drug Facts

Active ingredient

Sodium Chloride 0.65%

Uses

For dry nasal membranes squeeze twice in each nostril as needed.

Upright delivers a spray; Horizontally a stream; Upside down a drop.

Warnings

The use of this dispenser by more than one person may spread infection.

Directions

For dry nasal membranes squeeze twice in each nostril as needed.

Inactive ingredients

Purified Water, sodium chloride 0.65%, Disodium Phosphate, Phenylcarbinol, Monosodium Phosphate, Benzalkonium Chloride